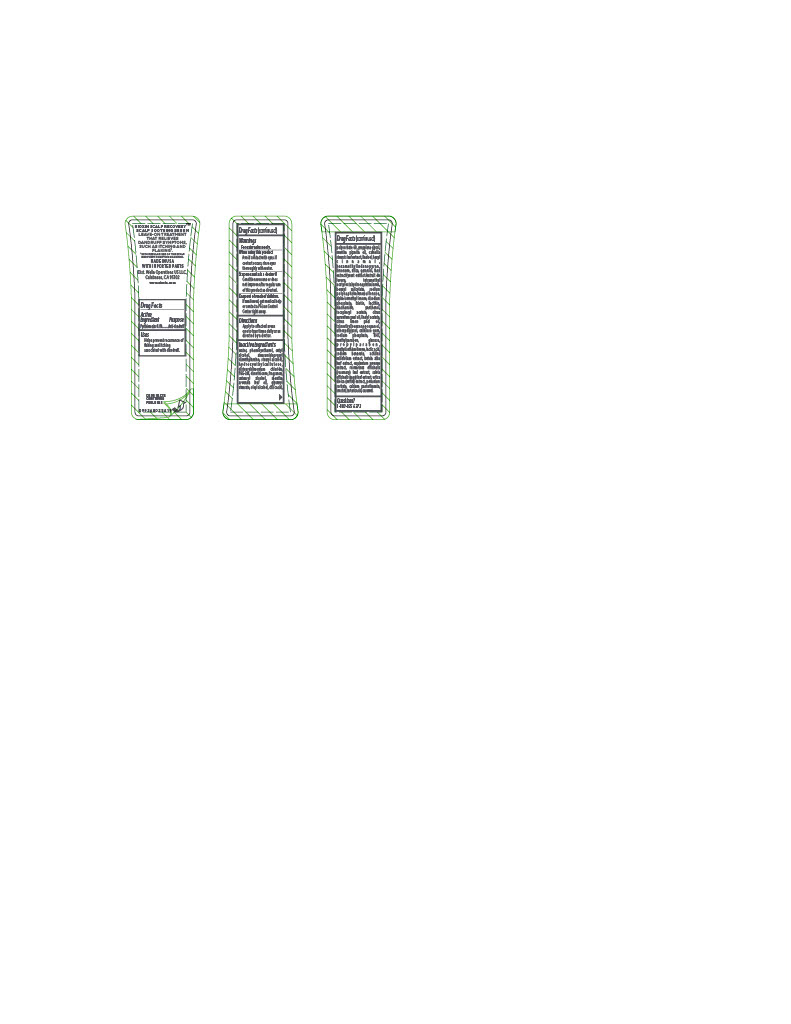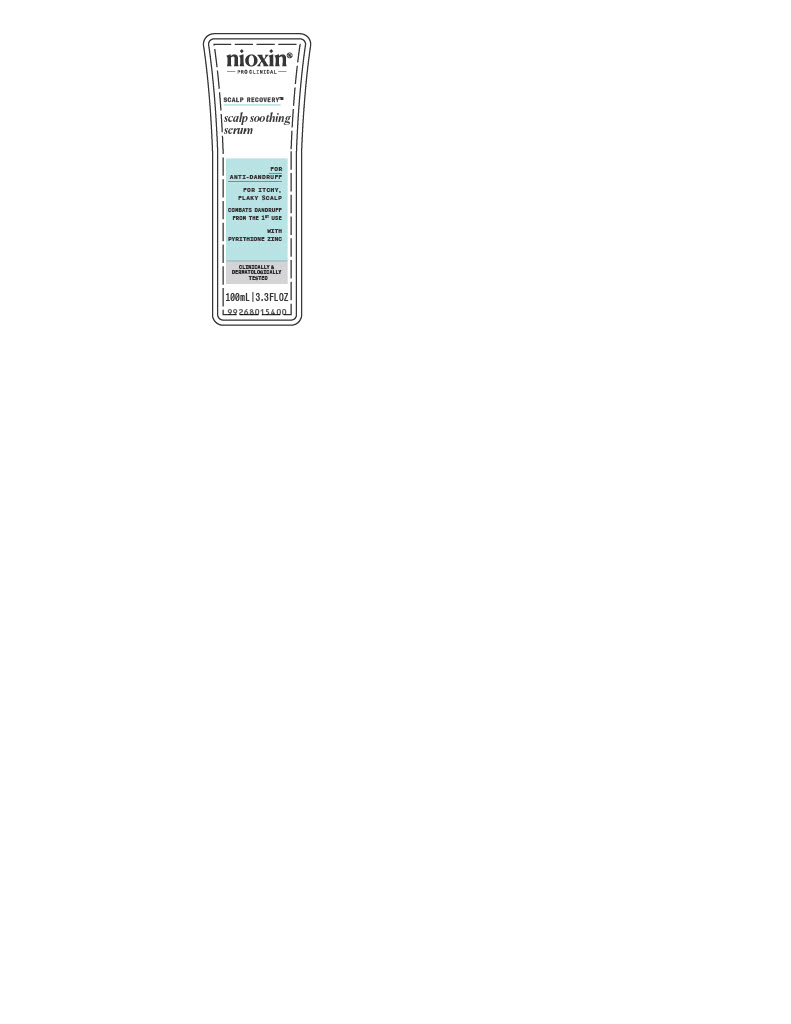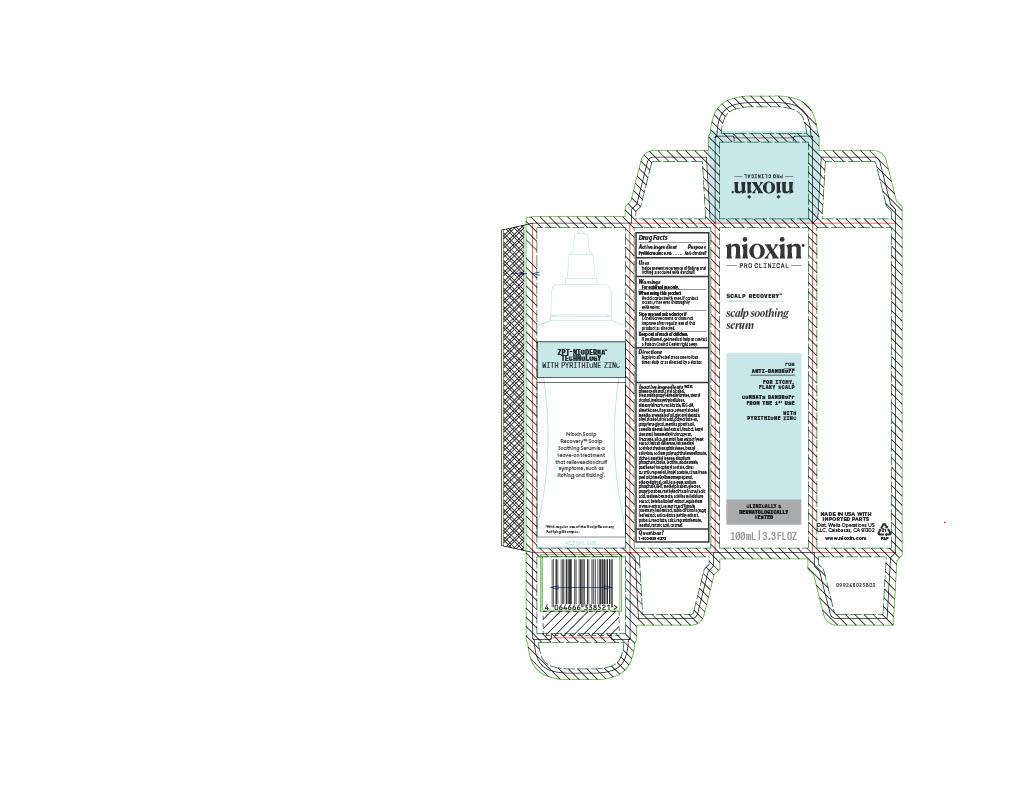 DRUG LABEL: nioxin PRO CLINICAL SCALP RECOVERY scalp soothing serum
NDC: 82157-015 | Form: LOTION
Manufacturer: The Wella Corporation
Category: otc | Type: HUMAN OTC DRUG LABEL
Date: 20251125

ACTIVE INGREDIENTS: PYRITHIONE ZINC 0.1 g/100 mL
INACTIVE INGREDIENTS: STEARAMIDOPROPYL DIMETHYLAMINE; CETEARYL ALCOHOL; LIMONENE, (+/-)-; DIMETHICONE; PROPYLENE GLYCOL; WATER; HYDROXYETHYLCELLULOSE; LINALOOL, (+/-)-; BENZYL SALICYLATE; FORMALDEHYDE/SODIUM NAPHTHALENESULFONATE COPOLYMER (3000 MW); BIOTIN; LECITHIN, SOYBEAN; PANTHENOL; CARAMEL; POLYSORBATE 60; CITRUS AURANTIUM PEEL OIL; TRIMETHYLBENZENEPROPANOL; GLUCOSE; INOSITOL; METHYLISOTHIAZOLINONE; BETULA ALBA LEAF; DISODIUM PHOSPHATE; HEXAMETHYLINDANOPYRAN; GERANIOL; ALPHA-ISOMETHYL IONONE; NIACINAMIDE; .ALPHA.-TOCOPHEROL ACETATE, D-; CELLULOSE GUM; ROSEMARY; MENTHA ARVENSIS LEAF OIL; YEAST, UNSPECIFIED; TETRAMETHYL ACETYLOCTAHYDRONAPHTHALENES; LINALYL ACETATE; CITRUS LIMON (LEMON) PEEL OIL; ETHOXYDIGLYCOL; SODIUM PHOSPHATE; METHYLPARABEN; PROPYLPARABEN; SODIUM BENZOATE; OLEYL ALCOHOL; SAGE; URTICA DIOICA LEAF; CALCIUM PANTOTHENATE; TARTARIC ACID; POTASSIUM SORBATE; LACTIC ACID; CITRIC ACID; BHT; ACHILLEA MILLEFOLIUM; MENTHA PIPERITA (PEPPERMINT) OIL; CETYL ALCOHOL; PHENOXYETHANOL; GLYCERYL STEARATE; CAMELLIA SINENSIS LEAF; HEXYL CINNAMAL; STEARYL ALCOHOL; SILICA; EQUISETUM ARVENSE BRANCH; DISTEARYLDIMONIUM CHLORIDE; PEG-2M

nioxin PRO CLINICAL SCALP RECOVERY scalp soothing serum

Drug Facts

Active Ingredient

Pyrithione zinc 0.1%

Purpose

Anti-Dandruff

Uses

- helps prevent recurrence of flaking and itching associated with dandruff.

Warnings

For external use only.

When using this product

- Avoid contact with eyes. If contact occurs, rinse eyes thoroughly with water.

Stop use and ask a doctor if

- Condition worsens or does not improve after regular use of this product as directed.

Keep out of reach of children. If swallowed, get medical help or contact a Poison Control Center right away.

Directions

- Apply to affected areas one to four times daily or as directed by a doctor.

INACTIVE INGREDIENT

Inactive ingredients water, phenoxyethanol, cetyl alcohol, stearamidopropyl dimethylamine, stearyl alcohol, hydroxyethylcellulose, distearyldimonium chloride, PEG-2M, dimethicone, fragrance, cetearyl alcohol, mentha arvensis leaf oil, glyceryl stearate, oleyl alcohol, citric acid, polysorbate 60, propylene glycol, mentha piperita oil, camellia sinensis leaf extract, linalool, hexyl cinnamal, hexamethylindanopyran, limonene, silica, geraniol, faex extract/yeast extract/extrait de levure, tetramethyl acetyloctahydronaphthalenes, benzyl salicylate, sodium polynaphthalenesulfonate, alpha-isomethyl ionone, disodium phosphate, biotin, lecithin, niacinamide, panthenol, tocopheryl acetate, citrus aurantium peel oil, linalyl acetate, citrus limon peel oil, trimethylbenzenepropanol, ethoxydiglycol, cellulose gum, sodium phosphate, BHT, methylparaben, glucose, propylparaben, methylisothiazolinone, lactic acid, sodium benzoate, achillea millefolium extract, betula alba leaf extract, equisetum arvense extract, rosmarinus officinalis (rosemary) leaf extract, salvia officinalis (sage) leaf extract, urtica dioica (nettle) extract, potassium sorbate, calcium pantothenate, inositol, tartaric acid, caramel.

Questions?
1-800-935-5273

NIOXIN SCALP RECOVERY™

SCALP SOOTHING SERUM

LEAVE-ON TREATMENT THAT RELIEVES DANDRUFF SYMPTOMS, SUCH AS ITCHING AND FLAKING^1
^1WITH REGULAR USE OF THE SCALP RECOVERY PURIFYING SHAMPOO.

Made in USA WITH IMPORTED PARTS

Dist Wella Operations US LLC. Calabasas, CA 91302

www.nioxin.com

PACKAGE LABEL

nioxin®

PRO CLINICAL

SCALP RECOVERYTM

scalp soothing serum

FOR ANTI-DANDRUFF

FOR ITCHY FLAKY SCALP

COMBATS DANDRUFF FROM THE 1ST USE

WITH PYRITHIONE ZINC

CLINICALLY & DERMATOLOGICALLY TESTED

100 mL | 3.3 FL OZ